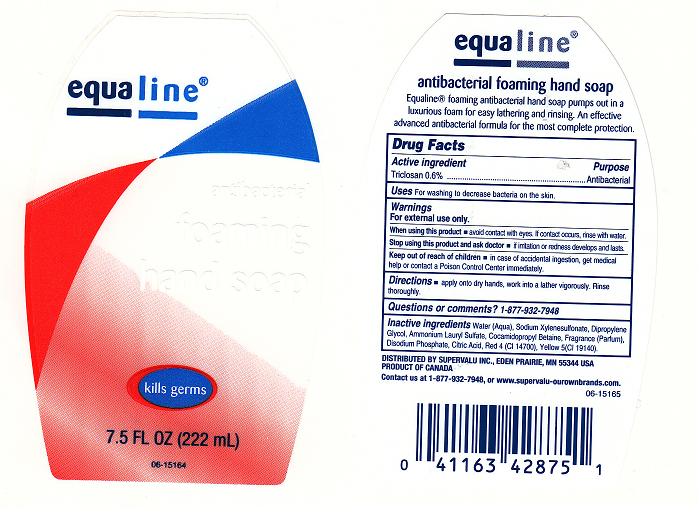 DRUG LABEL: ANTIBACTERIAL FOAMING 
NDC: 41163-168 | Form: LIQUID
Manufacturer: SUPERVALU INC
Category: otc | Type: HUMAN OTC DRUG LABEL
Date: 20111024

ACTIVE INGREDIENTS: TRICLOSAN 0.6 mL/100 mL
INACTIVE INGREDIENTS: WATER; SODIUM  XYLENESULFONATE; DIPROPYLENE GLYCOL; AMMONIUM LAURYL SULFATE; COCAMIDOPROPYL BETAINE; SODIUM PHOSPHATE, DIBASIC, DIHYDRATE; CITRIC ACID MONOHYDRATE; FD&C RED NO. 4; FD&C YELLOW NO. 5

DRUG FACTS

Active Ingredient

Triclosan 0.6%

Purpose

Antibacterial

Uses

For washing to decrease bacteria on the skin.

Warnings

For external use only.

When using this product

Avoid contact with eyes. If contact occurs, rinse with water.

Stop using this product and ask doctor if

Irritation or redness develops and lasts.

Keep out of reach of children

In case of accidental ingestion, get medical help and contact a Poison Control Center immediately.

Directions

Apply onto wet hands, work into a lather vigorously. Rinse thoroughly.

Questions or Comments

1-877-932-7948

Inactive Ingredients

WATER, SODIUMXYLENE SULFONATE, DIPROPYLENE GLYCOL, AMMONIUM LAURYL SULFATE, COCAMIDOPROPYL BETAINE, FRAGRANCE, DISODIUM PHOSPHATE, CITRIC ACID, RED 4 (CI 14700), YELLOW 5 (CI 19140).